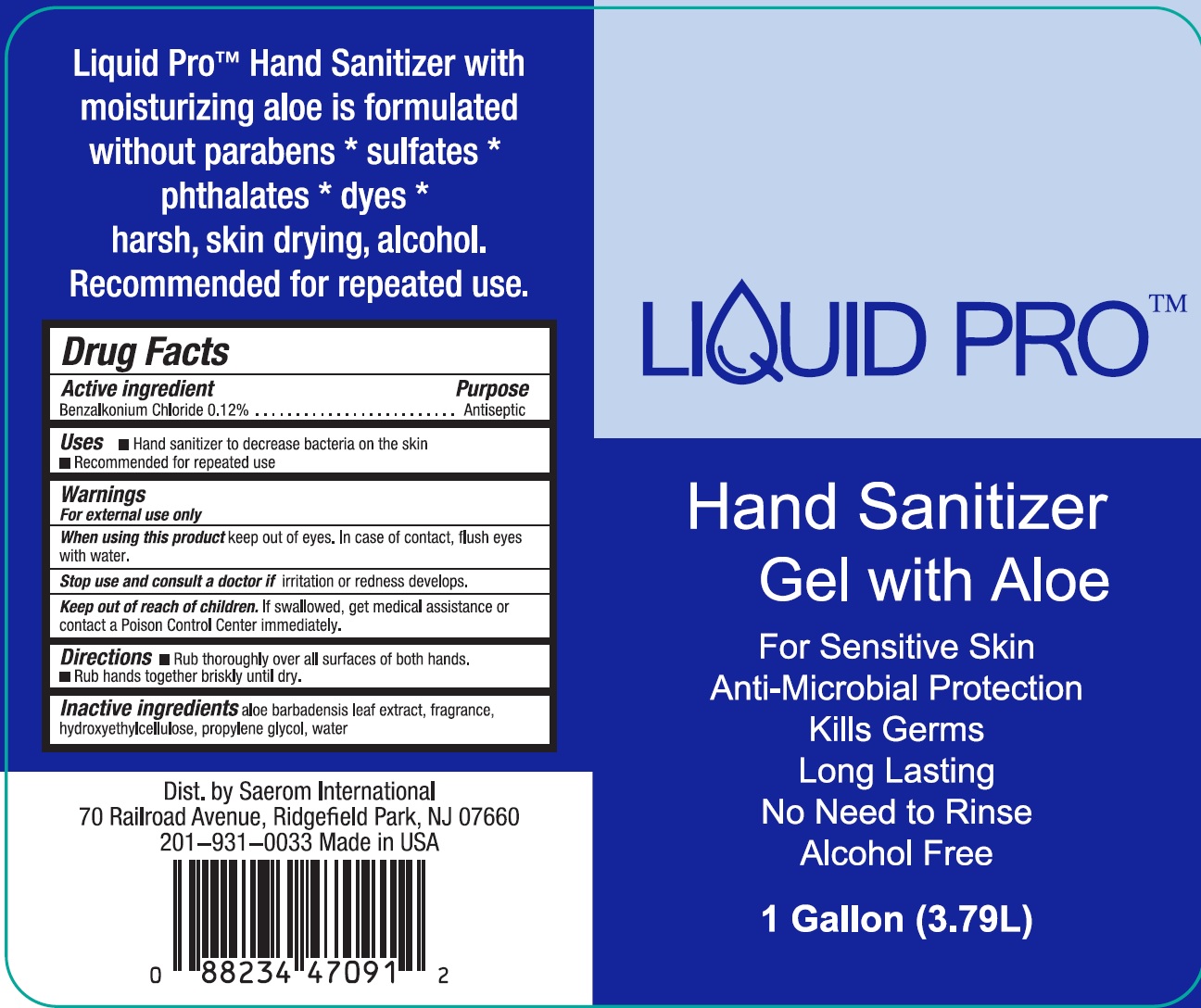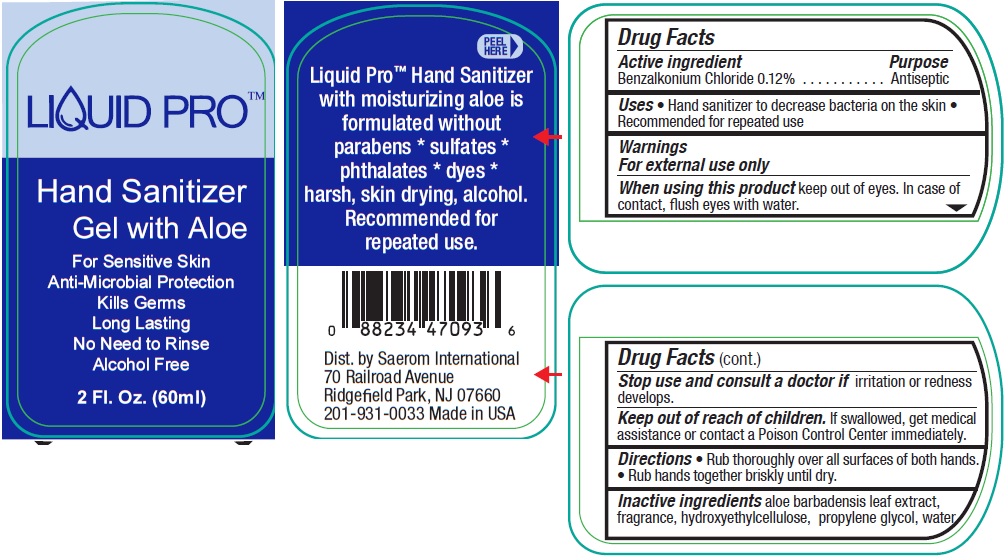 DRUG LABEL: Liquid Pro Hand Sanitizer
NDC: 75774-000 | Form: GEL
Manufacturer: Saerom International, Inc.
Category: otc | Type: HUMAN OTC DRUG LABEL
Date: 20200429

ACTIVE INGREDIENTS: BENZALKONIUM CHLORIDE 1.2 mg/1 mL
INACTIVE INGREDIENTS: ALOE VERA LEAF; HYDROXYETHYL CELLULOSE, UNSPECIFIED; PROPYLENE GLYCOL; WATER

Liquid Pro Hand Sanitizer Gel

Active ingredient

Benzalkonium Chloride 0.12%

Purpose

Antiseptic

Uses

• Hand sanitizer to decrease bacteria on the skin • Recommended for repeated use

Warnings

For external use only

When using this product

keep out of eyes. In case of contact, flush eyes with water.

Stop use and consult a doctor if

irritation or redness develops.

Keep out of reach of children.

If swallowed, get medical assistance or contact a Poison Control Center immediately.

Directions

• Rub thoroughly over all surfaces of both hands.
• Rub hands together briskly until dry.

Inactive ingredients

aloe barbadensis leaf extract, fragrance, hydroxyethylcellulose, propylene glycol, water